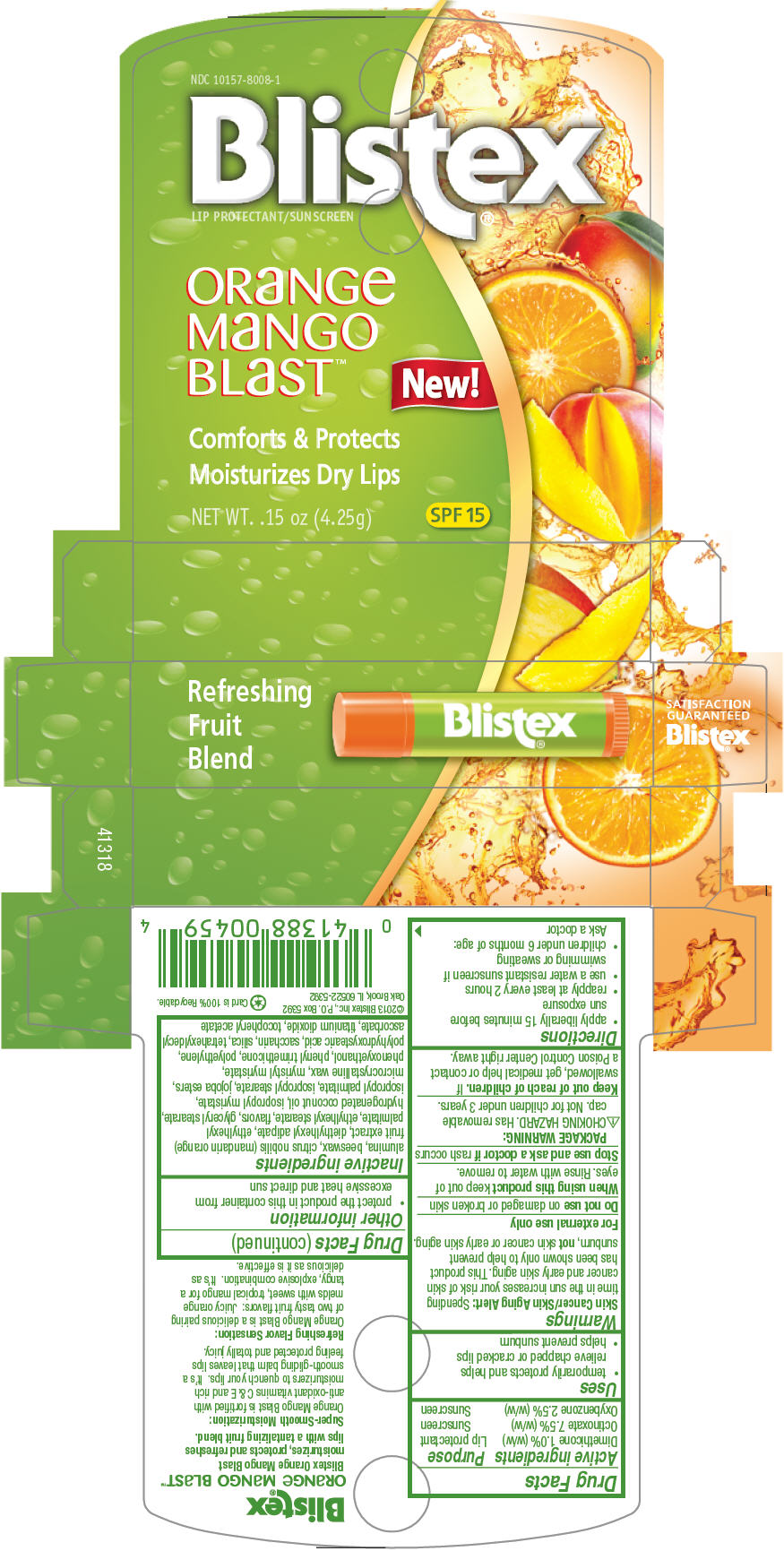 DRUG LABEL: Blistex 
NDC: 10157-8008 | Form: STICK
Manufacturer: Blistex Inc.
Category: otc | Type: HUMAN OTC DRUG LABEL
Date: 20140102

ACTIVE INGREDIENTS: Dimethicone 1 g/100 g; Octinoxate 7.5 g/100 g; Oxybenzone 2.5 g/100 g
INACTIVE INGREDIENTS: Microcrystalline Wax; Hydrogenated Coconut Oil; Ethylhexyl Palmitate; Ethylhexyl Stearate; Diethylhexyl Adipate; Isopropyl Palmitate; Isopropyl Myristate; Isopropyl Stearate; Tangerine; Yellow Wax; Glyceryl Monostearate; Myristyl Myristate; Phenyl Trimethicone; Phenoxyethanol; Titanium Dioxide; Aluminum Oxide; Silicon Dioxide; Saccharin; .Alpha.-Tocopherol Acetate; High Density Polyethylene; Tetrahexyldecyl Ascorbate

Blistex®
Orange Mango Blast™

Drug Facts

ACTIVE INGREDIENT

Active ingredients | Purpose
Dimethicone 1.0% (w/w) | Lip protectant
Octinoxate 7.5% (w/w) | Sunscreen
Oxybenzone 2.5% (w/w) | Sunscreen

Uses

- temporarily protects and helps relieve chapped or cracked lips
- helps prevent sunburn

Warnings

Skin Cancer/Skin Aging Alert

Spending time in the sun increases your risk of skin cancer and early skin aging. This product has been shown only to help prevent sunburn, not skin cancer or early skin aging.

For external use only

Do not use on damaged or broken skin

When using this product keep out of eyes. Rinse with water to remove.

Stop use and ask a doctor if rash occurs

PACKAGE WARNING

CHOKING HAZARD. Has removable cap. Not for children under 3 years.

Keep out of reach of children. If swallowed, get medical help or contact a Poison Control Center right away.

Directions

- apply liberally 15 minutes before sun exposure
- reapply at least every 2 hours
- use a water resistant sunscreen if swimming or sweating
- children under 6 months of age: Ask a doctor

Other information

- protect the product in this container from excessive heat and direct sun

Inactive ingredients

alumina, beeswax, citrus nobilis (mandarin orange) fruit extract, diethylhexyl adipate, ethylhexyl palmitate, ethylhexyl stearate, flavors, glyceryl stearate, hydrogenated coconut oil, isopropyl myristate, isopropyl palmitate, isopropyl stearate, jojoba esters, microcrystalline wax, myristyl myristate, phenoxyethanol, phenyl trimethicone, polyethylene, polyhydroxystearic acid, saccharin, silica, tetrahexyldecyl ascorbate, titanium dioxide, tocopheryl acetate

PRINCIPAL DISPLAY PANEL - 4.25 g Cylinder Carton

NDC 10157-8008-1

BLISTEX®
LIP PROTECTANT/SUNSCREEN

ORANGE
MANGO
BLAST™

New!

Comforts & Protects
Moisturizes Dry Lips

NET WT. .15 oz (4.25g)

SPF 15